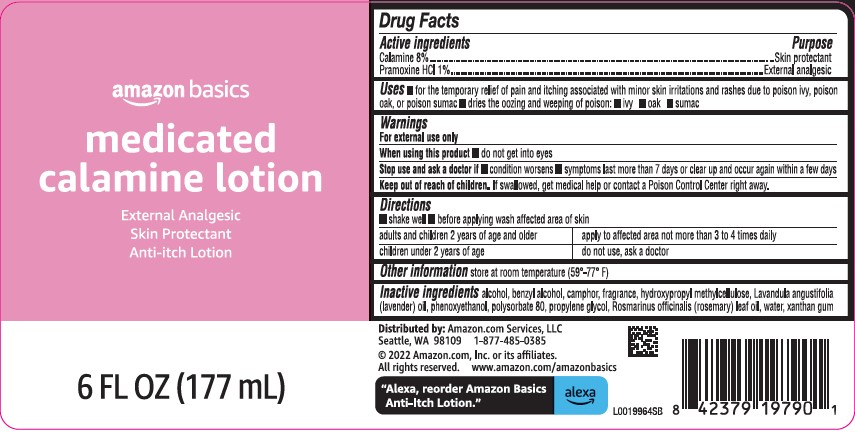 DRUG LABEL: Calamine
NDC: 72288-436 | Form: LOTION
Manufacturer: Amazon.Com Services LLC
Category: otc | Type: HUMAN OTC DRUG LABEL
Date: 20250519

ACTIVE INGREDIENTS: FERRIC OXIDE RED 80 mg/1 mL; PRAMOXINE HYDROCHLORIDE 10 mg/1 mL
INACTIVE INGREDIENTS: ALCOHOL; BENZYL ALCOHOL; CAMPHOR (NATURAL); HYPROMELLOSE, UNSPECIFIED; LAVENDER OIL; PHENOXYETHANOL; POLYSORBATE 80; PROPYLENE GLYCOL; ROSEMARY OIL; WATER; XANTHAN GUM

Basics 336.003/336AG
Medicated Calamine Anti-Itch Lotion

Active ingredients

Calamine 8%

Pramoxine HCl 1%

Purpose

Skin protectant

External analgesic

Uses

- for the temporary relief of pain and itching associated with minor skin irritations and rashes due to poison ivy, poison oak, or poison sumac
- dries the oozing and weeping of poison:
- ivy
- oak
- sumac

Warnings

For external use only

When using this product

- do not get into eyes

Stop use and ask a doctor

- condition worsens
- symptoms last more than 7 days or clean up and occur again within a few days

Keep out of reach of children.

If swallowed, get medical help or contact a Poison Control Center right away.

Directions

- shake well
- before applying was affected are of skin

Adults and children 2 years of age and older - apply to affected area not more than 3 to 4 times daily

Children under 2 years of age - do not use, ask a doctor

Other information

store at room temperature (59°-77°F)

Inactive ingredients

alcohol, benzyl alcohol, camphor, fragrance, hydroxypropyl methylcellulose, Lavandula angustifolia (lavender) oil, phenoxyethanol, polysorbate 80, propylene glycol, Rosmarinus officinalis (rosemary) leaf oil, water, xanthan gum

ADVERSE REACTION

DISTRIBUTED BY: Amazon.com, Services, LLC

Seattle, WA 98109 1-877-485-0385

2022 Amazon.com, Inc. or its affiliated.

All rights reserved. www.amazon.com/amazonbasics

"Alexa, reorder Amazon Basics Anti-Itch Lotion." alexa

Principal display panel

amazon basics

medicated

calamine lotion

External Analgesic

Skin Protectant

Anti-itch lotion

6 FL OZ (177 mL)